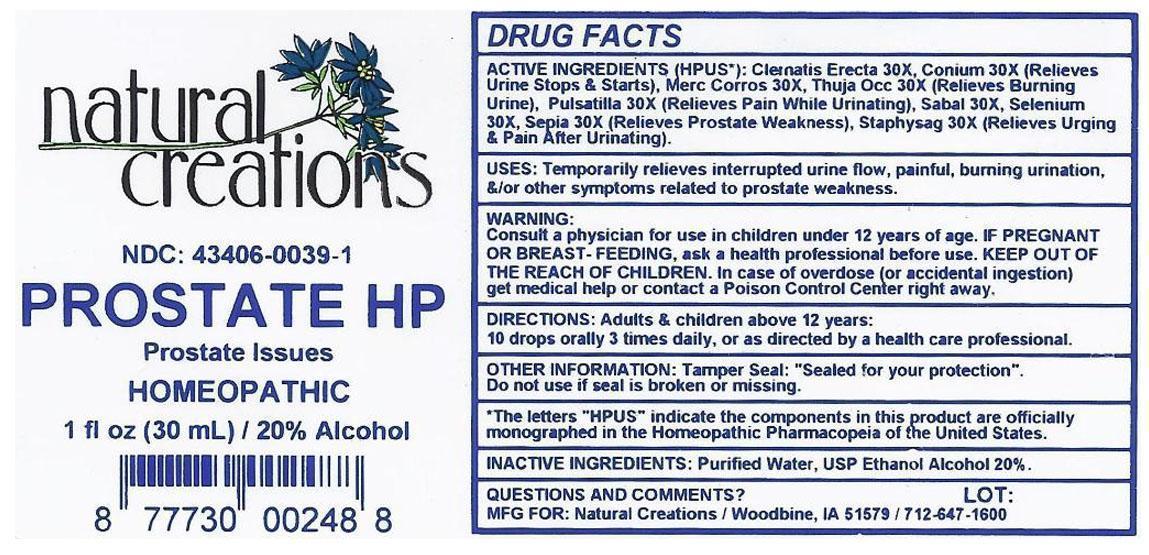 DRUG LABEL: PROSTATE HP
NDC: 43406-0039 | Form: LIQUID
Manufacturer: Natural Creations, Inc.
Category: homeopathic | Type: HUMAN OTC DRUG LABEL
Date: 20121112

ACTIVE INGREDIENTS: CLEMATIS RECTA FLOWERING TOP 30 [hp_X]/1 mL; CONIUM MACULATUM FLOWERING TOP 30 [hp_X]/1 mL; LYCOPODIUM CLAVATUM SPORE 30 [hp_X]/1 mL; MERCURIC CHLORIDE 30 [hp_X]/1 mL; PULSATILLA VULGARIS 30 [hp_X]/1 mL; SAW PALMETTO 30 [hp_X]/1 mL; SELENIUM 30 [hp_X]/1 mL; SEPIA OFFICINALIS JUICE 30 [hp_X]/1 mL; DELPHINIUM STAPHISAGRIA SEED 30 [hp_X]/1 mL; THUJA OCCIDENTALIS LEAFY TWIG 30 [hp_X]/1 mL
INACTIVE INGREDIENTS: WATER; ALCOHOL

PROSTATE HP

ACTIVE INGREDIENT

ACTIVE INGREDIENTS (HPUS*): Clematis Erecta 30X, Conium Maculatum 30X, Lycopodium Clavatum 30X, Mercurius Corrosivus 30X, Pulsatilla 30X, Sabal Serrulata 30X, Selenium Metallicum 30X, Sepia 30X, Staphysagria 30X, Thuja Occidentalis 30X

INDICATIONS AND USAGE

USES: Temporarily relieves interrupted urine flow, painful, burning urination, &/or other symptoms related to prostate weakness.

WARNING:

Consult a physician for use in children under 12 years of age. IF PREGNANT OR BREAST-FEEDING< ask a health care professional before use. KEEP OUT OF THE REACH OF CHILDREN. In case of overdose (or accidental ingestion) get medical help or contact a Poison Control Center right away.

DOSAGE AND ADMINISTRATION

DIRECTIONS: Adults and children above 12 years: 10 drops orally 3 times daily, or as directed by a health care professional.

OTHER INFORMATION: Tamper Seal: "Sealed for your protection."

Do not use if seal is broken or missing.

REFERENCES

*The letters "HPUS" indicate the components in the product are officially monographed in the Homeopathic Pharmacopeia of the United States.

INACTIVE INGREDIENTS: Purified Water, USP Ethanol Alcohol 20%

QUESTIONS AND COMMENTS?

MFG FOR: Natural Creations / Woodbine, IA / 51579 712.647.1600

LOT:

PURPOSE

USES: Temporarily relieves interrupted urine flow, painful, burning urination, &/or other symptoms related to prostate weakness.

KEEP OUT OF REACH OF CHILDREN

KEEP OUT OF THE REACH OF CHILDREN. In case of overdose (or accidental ingestion) get medical help or contact a Poison Control Center.

PACKAGE LABEL

NDC: 43406-0039-1

PROSTATE HP

Prostate Issues

HOMEOPATHIC

1 fl oz (30 mL) / 20% Alcohol

UPC: 877730002488